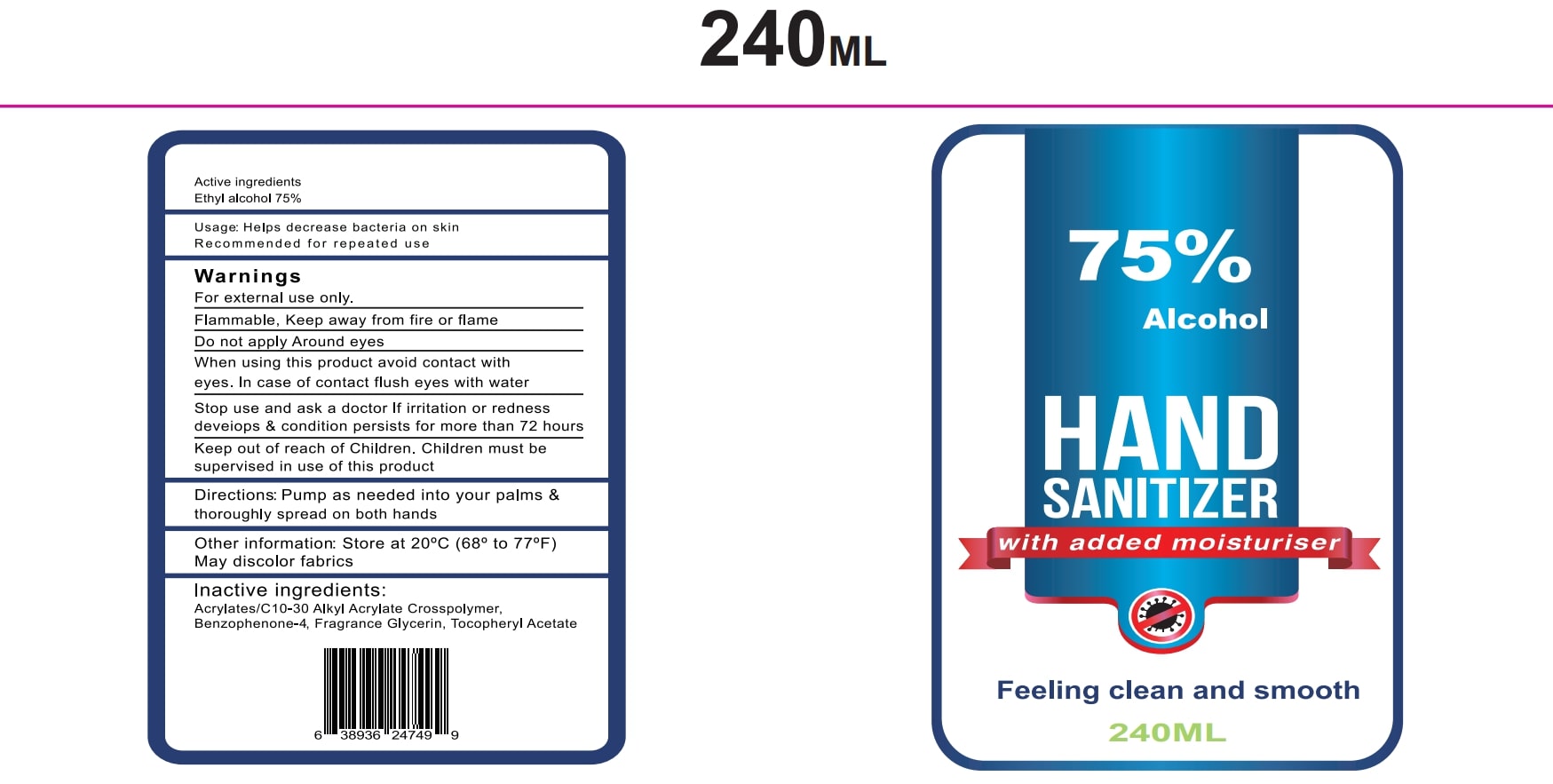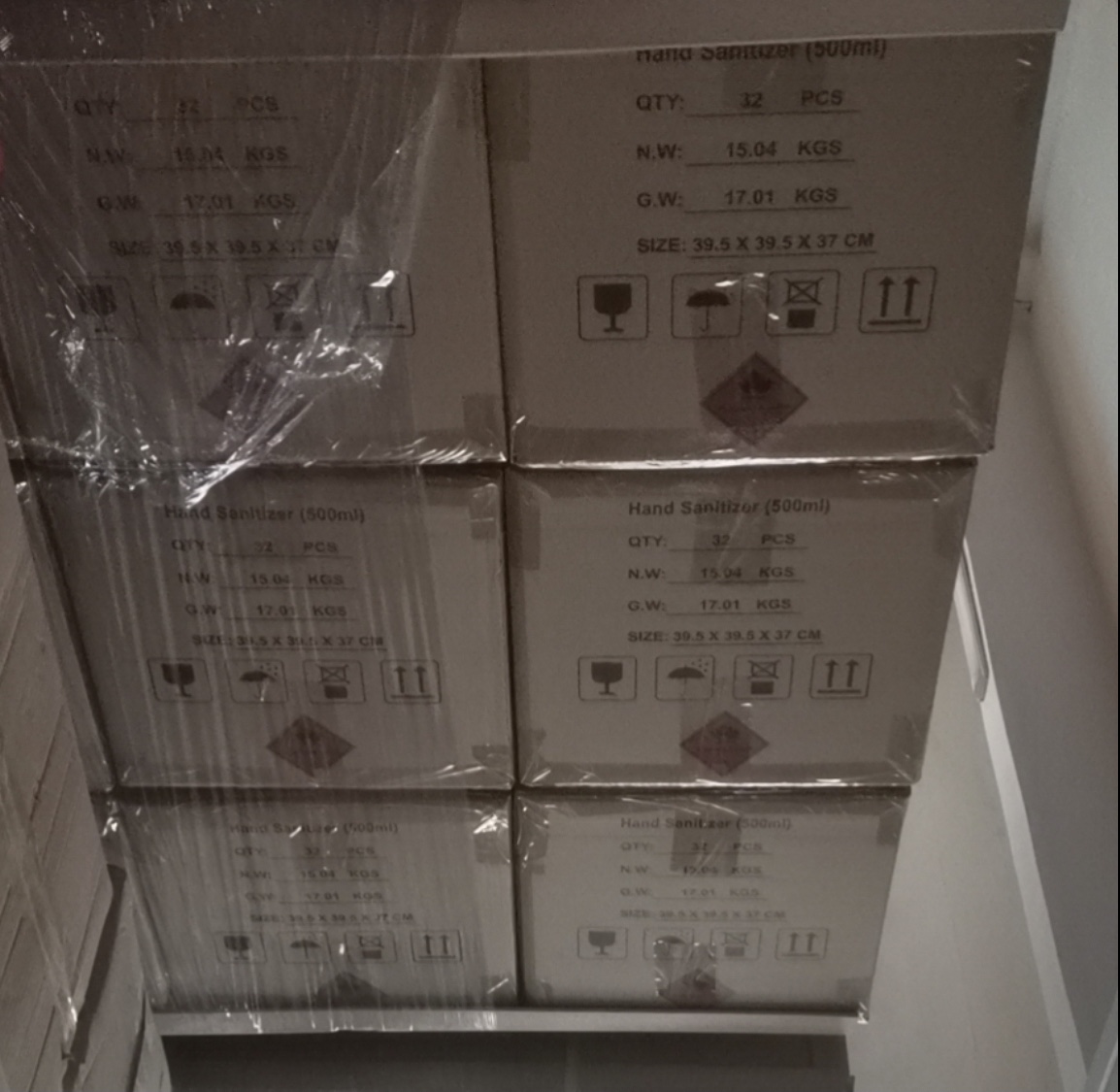 DRUG LABEL: Hand Sanitizer
NDC: 81011-128 | Form: GEL
Manufacturer: Design Element Group INC
Category: otc | Type: HUMAN OTC DRUG LABEL
Date: 20201014

ACTIVE INGREDIENTS: ALCOHOL 75 mL/100 mL
INACTIVE INGREDIENTS: WATER; FRAGRANCE FRESHWATER CUCUMBER ORC2000871; ACRYLATES/VINYL ISODECANOATE CROSSPOLYMER (10000 MPA.S NEUTRALIZED AT 0.5%); SULISOBENZONE; .ALPHA.-TOCOPHEROL ACETATE

ACTIVE INGREDIENT

Ethyl Alcohol 75%

Stop use and ask a doctor if irritation or redness develops & condition persists for more than 72 hours.

Do no apply around eyes.

When using this product avoid contact with eyes. In case of contact flush eyes with water.

Keep out of reach of children.

Children must be supervised in use of this product.

PURPOSE

Helps decrease bacteria on skin.

Recommended for repeated use.

Stop use and ask a doctor if irriation or redness develops & condition persists for more than 72 hours.

When using this product avoid contact with eyes. In case of contact flush eyes with water.

OTHER SAFETY INFORMATION

Store at 20 C(68-77 F)

May discolor fabrics

STORAGE AND HANDLING

Store at 20 C (68-77F)

INACTIVE INGREDIENT

Acrylates/C10-30 Alkyl Acrylate Crosspolymer, Benzophenone-4, Fragrance Glycerin, Tocopheryl Acetate

WARNINGS

For external use only.

Flammable. Keep away from fire or flame.

Do not apply around eyes.

INSTRUCTIONS FOR USE

Pump as needed into your palms & thoroughly spread on both hands.

DOSAGE AND ADMINISTRATION

Active 75% ethyl alcohol

INDICATIONS AND USAGE

Help decrease bacteria on skin.

Pump as needed into your palms & thoroughly spread on both hands.

hand sanitizer gel

75% active ethyl alcohol

inactive ingredients

acrylate crosspolymer

benzophenone-4

fragrance glycerin

tocopheryl acetate

PACKAGE LABEL

75% Alcohol

Hand sanitizer with added moisturiser

Feeling clean and smooth